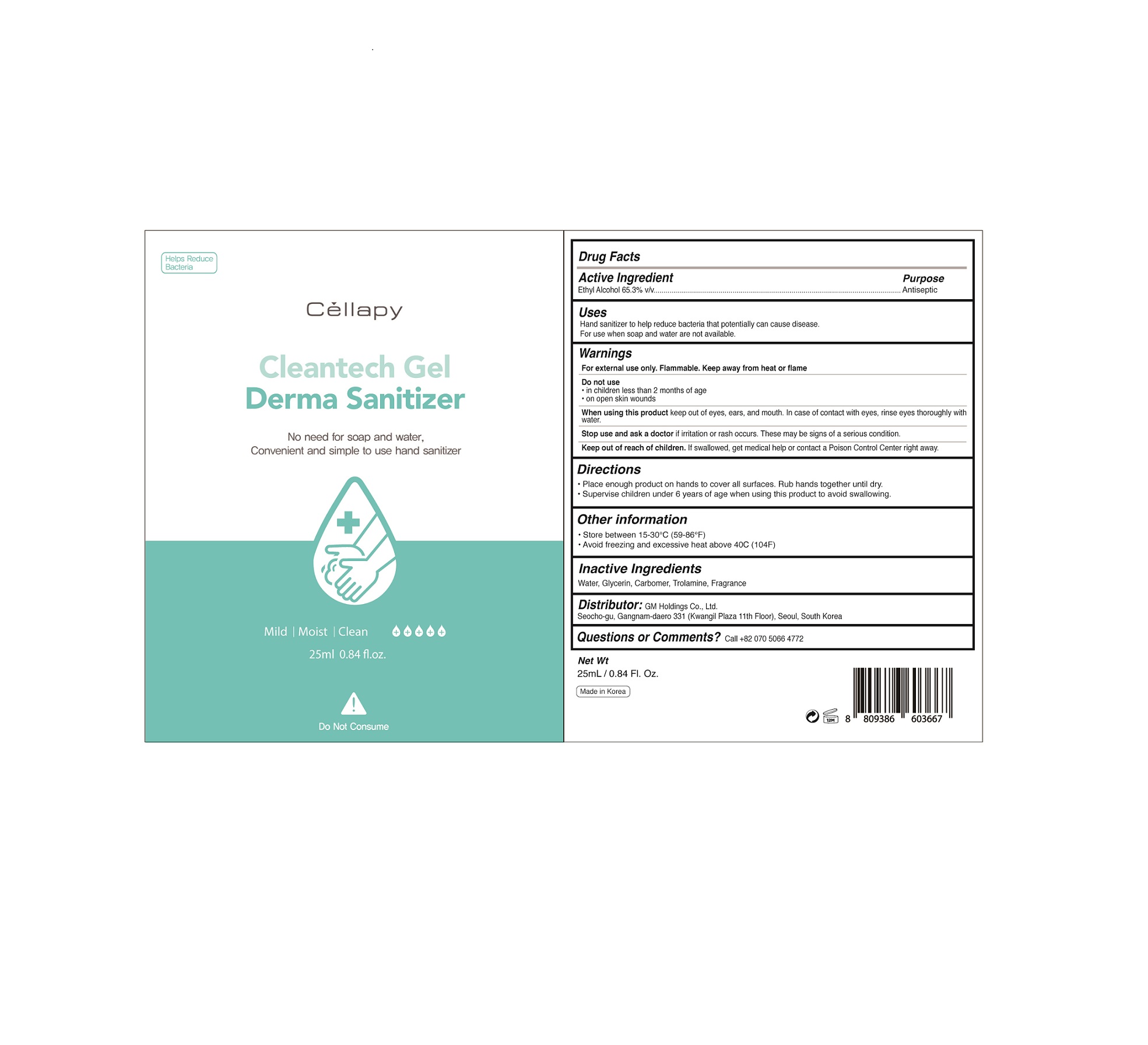 DRUG LABEL: Cellapy Cleantech Derma Sanitizer-alcohol-gel
NDC: 69278-115 | Form: GEL
Manufacturer: GM Holdings Co., Ltd
Category: otc | Type: HUMAN OTC DRUG LABEL
Date: 20200421

ACTIVE INGREDIENTS: ALCOHOL 65.3 mL/100 mL
INACTIVE INGREDIENTS: CARBOMER 934; TROLAMINE; WATER; GLYCERIN

Drug Facts

ACTIVE INGREDIENT

ethanol (alcohol) 65.3 v/v%

INACTIVE INGREDIENT

glycerin, carbomer, trolamine, combination spices, water

PURPOSE

Antiseptic

instant healthcare personnel hand antiseptic to reduce bacteria that potentially can cause disease

instant hand antiseptic to decrease bacteria on the skin
recommended for repeated use

KEEP OUT OF REACH OF THE CHILDREN

INDICATIONS AND USAGE

Apply to clean, dry hands. Apply sufficient amount to thoroughly wet all surfaces of hands and fingers. Rub onto hands until dry.

Supervise children in the use of this product.

WARNINGS

For external use only.

Flammable, keep away from fire or flame.

When using this product keep out of eyes. If contact with eyes occurs, rinse promptly and thoroughly with water.

Stop use and ask a doctor if significant irritation or sensitization develops.

Keep out of reach of children. If swallowed, get medical help or contact a Poison Control Center right away.

DOSAGE AND ADMINISTRATION

Pour a small amount into hands, spread evenly and rub into the skin